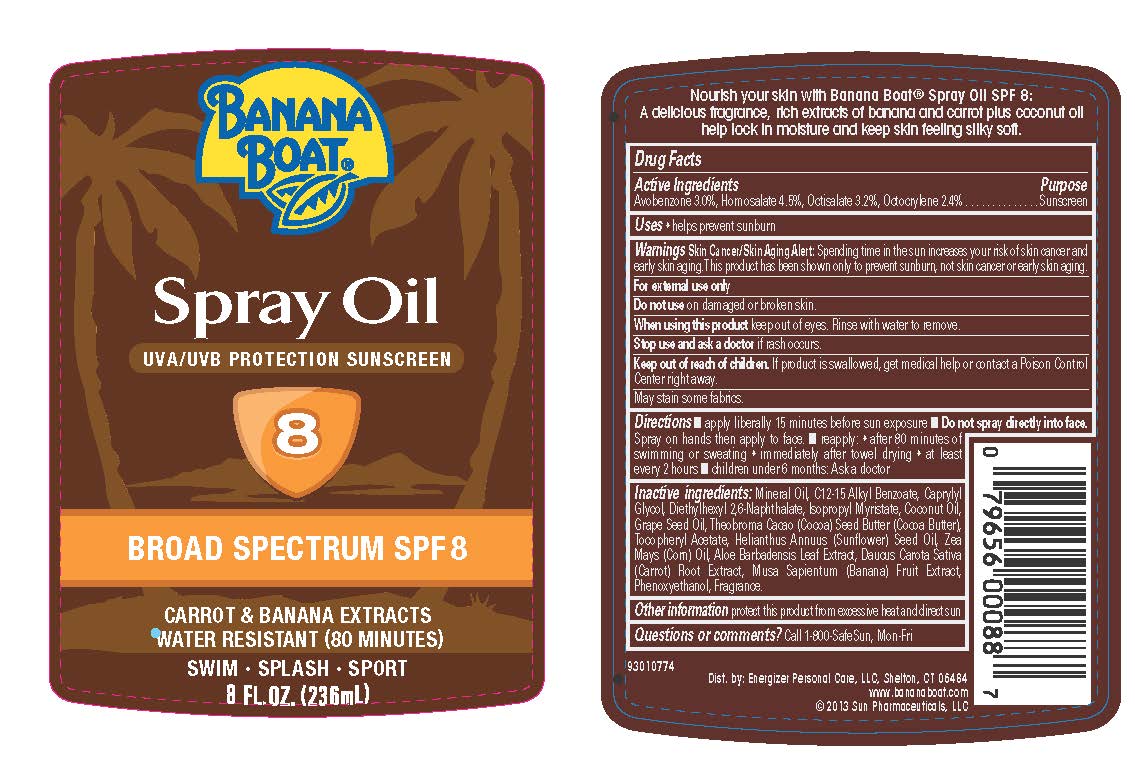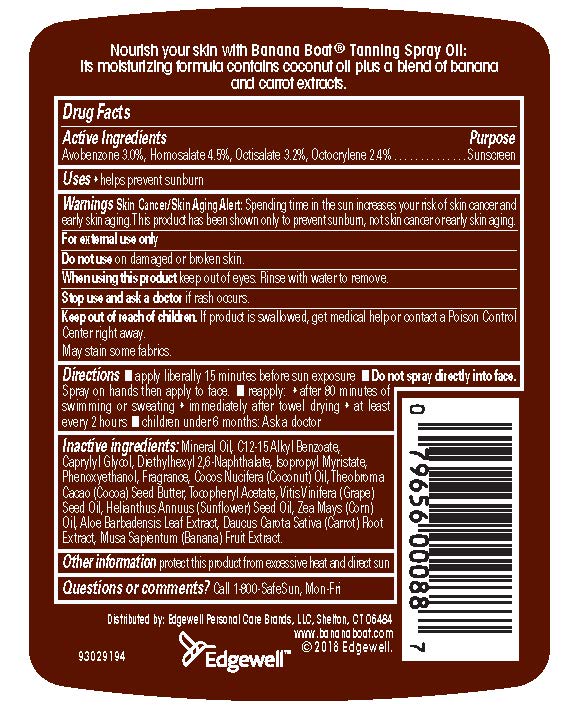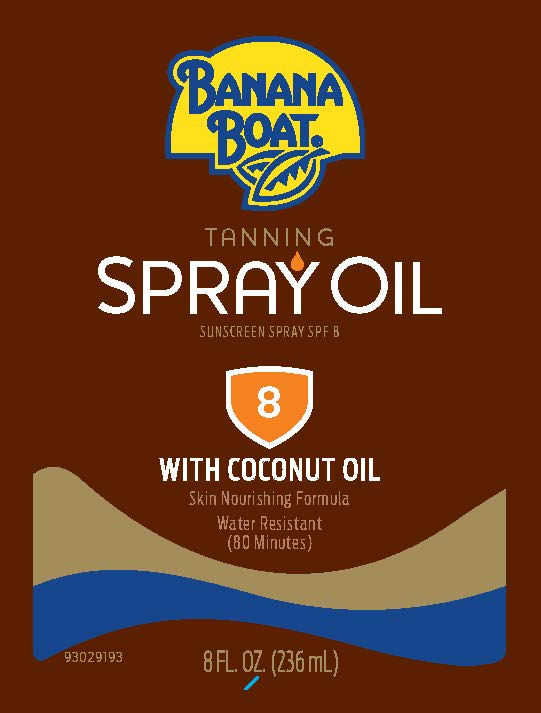 DRUG LABEL: Banana Boat
NDC: 63354-410 | Form: OIL
Manufacturer: Edgewell Personal Care Brands, LLC
Category: otc | Type: HUMAN OTC DRUG LABEL
Date: 20221121

ACTIVE INGREDIENTS: HOMOSALATE 4.5 g/100 g; OCTISALATE 3.2 g/100 g; OCTOCRYLENE 2.4 g/100 g; AVOBENZONE 3 g/100 g
INACTIVE INGREDIENTS: MINERAL OIL; CAPRYLYL GLYCOL; DIETHYLHEXYL 2,6-NAPHTHALATE; ISOPROPYL MYRISTATE; COCONUT OIL; GRAPE SEED OIL; THEOBROMA CACAO WHOLE; .ALPHA.-TOCOPHEROL ACETATE; ALOE VERA LEAF; SUNFLOWER OIL; CORN OIL; CARROT; BANANA; PHENOXYETHANOL

Active ingredients

Avobenzone 3.0%, Homosalate 4.5%, Octisalate 3.2%, Octocrylene 2.4%

Purpose

Sunscreen

Uses

Helps prevent sunburn

Warnings

For external use only

Skin Cancer/Skin Aging Alert: Spending time in the sun increases your risk of skin cancer and early skin aging. This product has been shown only to help prevent sunburn, not skin cancer or early skin aging.

Do not use

on damaged or broken skin

When using this product

Keep out of eyes. Rinse with water to remove

stop use and ask a doctor

if rash occurs

Keep out of reach of children

If product is swallowed, get medical help or contact a Poison Control Center right away. May stain some fabrics

Directions

Apply liberally 15 minutes before sun exposure; • Do not spray directly into face. Spray on hands and then apply to face. •Reapply: •after 80 minutes of swimming or sweating •immediately after towel drying •at least every 2 hours •Children under 6 months: Ask a doctor

Inactive ingredients

Mineral Oil, C12-15 Alkyl Benzoate, Caprylyl Glycol, Diethylhexyl 2,6-Naphthalate, Isopropyl Myristate, Coconut Oil, Grape Seed Oil, Theobroma Cacao (Cocoa) Seed Butter (Cocoa Butter),Tocopheryl Acetate, Helianthus Annuus (Sunflower) Seed Oil, Zea Mays (Corn) Oil, Aloe Barbadensis Leaf Extract, Daucus Carota Sativa (Carrot) Root Extract, Musa Sapientum (Banana) Fruit Extract,Phenoxyethanol, Fragrance.

Other Information

protect this product from excessive heat and direct sun

Questions & comments?

Call 1-800-SafeSun, mon-fri

PACKAGE LABEL

BANANA

BOAT®

TANNING

SPRAY OIL

SUNSCREEN SPRAY SPF 8

8

WITH COCONUT OIL

Skin Nourishing Formula

Water Resistant

(80 Minutes)

8 FL. OZ. (236 mL)

BANANA

BOAT

Spray Oil

UVA/UVB PROTECTION SUNSCREEN

8

BROAD SPECTRUM SPF 8

CARROT & BANANA EXTRACTS

WATER RESISTANT (80 MINUTES)

SWIM SPLASH SPORT